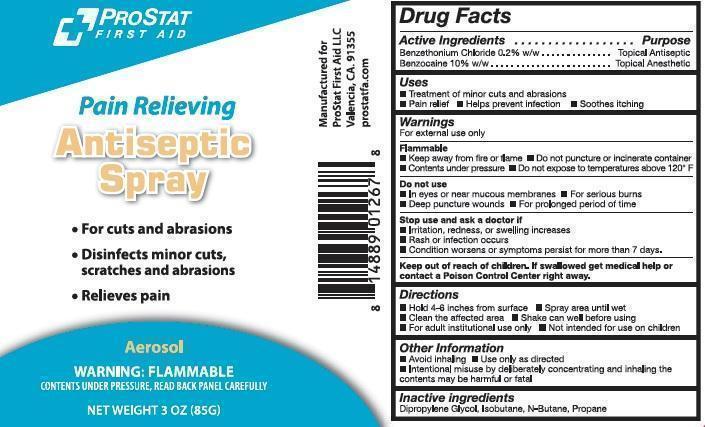 DRUG LABEL: ProStat Antiseptic First Aid
NDC: 58228-0104 | Form: AEROSOL, SPRAY
Manufacturer: ProStat First Aid
Category: otc | Type: HUMAN OTC DRUG LABEL
Date: 20140307

ACTIVE INGREDIENTS: BENZETHONIUM CHLORIDE 170 mg/85 g; BENZOCAINE 8500 mg/85 g
INACTIVE INGREDIENTS: DIPROPYLENE GLYCOL; ISOBUTANE; BUTANE; PROPANE

ProStat Antiseptic Spray

Active Ingredients

Benzethonium Chloride 0.2% w/w
Benzocaine 10% w/w

Purpose

Topical antiseptic
Topical anesthetic

Uses

Treatment of minor cuts and abrasions
Pain relief
Helps prevent infection
Soothes itching

Warnings

For external use only

Flammable
Keep away from fire or flame
Contents under pressure
Do not puncture or incinerate container
Do not expose to temperatures above 120° F

Do not use

In or eyes or near mucous membranes
For serious burns
Deep puncture wounds
For a prolonged period of time

Stop use and ask a doctor if

Irritation, redness, or swelling increases
Rash or infection occurs
Condition worsens or symptoms persist for more than 7 days.

Directions

Hold 4-6 inches from surface
Spray area until wet
Clean the affected area
Shake can well before using
For adult institutional use only
Not intended for use on children

Other information

Avoid inhaling
Use only as directed
Intentional misuse by deliberately concentrating and inhaling the contents may be harmful or fatal

Inactive ingredients

dipropylene glycol, isobutane, n-butane, propane